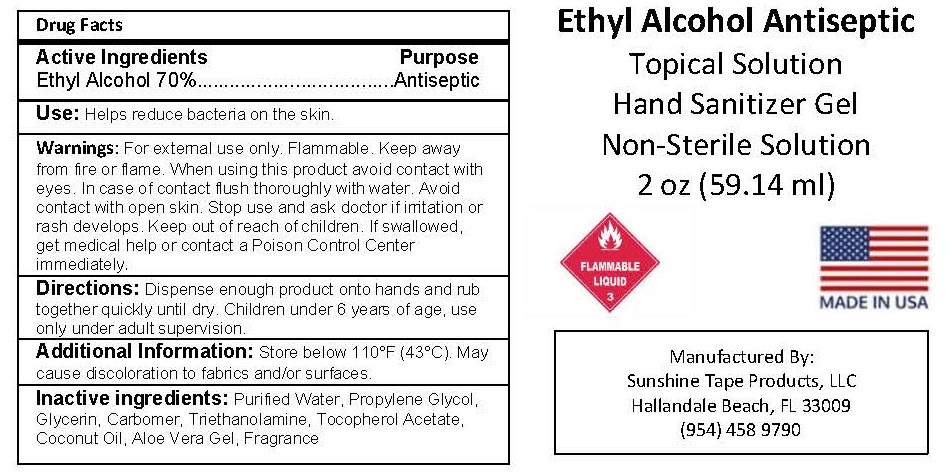 DRUG LABEL: HAND SANITIZER
NDC: 74598-112 | Form: GEL
Manufacturer: Sunshine Tape Products LLC
Category: otc | Type: HUMAN OTC DRUG LABEL
Date: 20200508

ACTIVE INGREDIENTS: ALCOHOL 70 mL/100 mL
INACTIVE INGREDIENTS: WATER; PROPYLENE GLYCOL; GLYCERIN; CARBOMER HOMOPOLYMER, UNSPECIFIED TYPE; TROLAMINE; .ALPHA.-TOCOPHEROL ACETATE; COCONUT OIL; ALOE VERA LEAF

HAND SANITIZER GEL - 70% ETHYL ALCOHOL

ACTIVE INGREDIENT

ETHYL ALCOHOL 70%

PURPOSE

ANTISEPTIC

USES

Helps reduce bacteria on the skin.

WARNINGS

For external use only. Flammable. Keep away from fire or flame. When using this product avoid contact with eyes. In case of contact flush thoroughly with water. Avoid contact with open skin. Stop use and ask doctor if irritation or rash develops.

Keep out of reach of children. If swallowed, get medical help or contact a Poison Control Center immediately.

DIRECTIONS

Dispense enough product onto hands and rub together quickly until dry. Children under 6 years of age, use only under adult supervision.

Additional Information:

Store below 110°F (43°C). May cause discoloration to fabrics and/or surfaces.

INACTIVE INGREDIENTS

Purified Water, Propylene Glycol, Glycerin, Carbomer, Triethanolamine, Tocopherol Acetate, Coconut Oil, Aloe Vera Gel, Fragrance